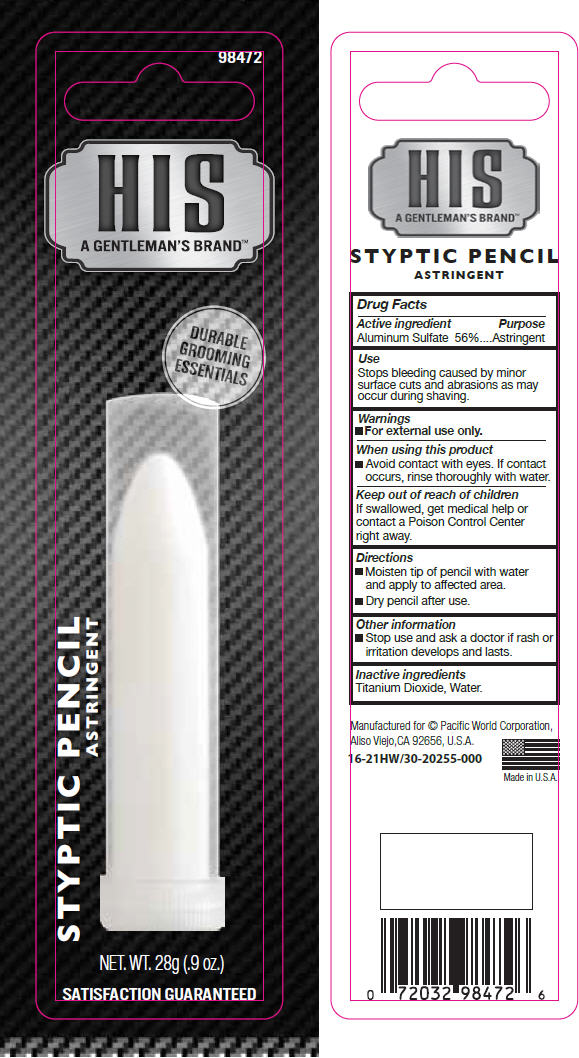 DRUG LABEL: HIS Styptic Pencil
NDC: 60193-501 | Form: STICK
Manufacturer: Pacific World Corporation
Category: otc | Type: HUMAN OTC DRUG LABEL
Date: 20141104

ACTIVE INGREDIENTS: Aluminum sulfate 5.6 g/10 g
INACTIVE INGREDIENTS: Titanium dioxide; Water

HIS Styptic Pencil

Drug Facts

Active ingredient

Aluminum Sulfate 56%

Purpose

Astringent

Use

Stops bleeding caused by minor surface cuts and abrasions as may occur during shaving.

Warnings

- For external use only.

When using this product

- Avoid contact with eyes. If contact occurs, rinse thoroughly with water.

Keep out of reach of children

If swallowed, get medical help or contact a Poison Control Center right away.

Directions

- Moisten tip of pencil with water and apply to affected area.
- Dry pencil after use.

Other information

- Stop use and ask a doctor if rash or irritation develops and lasts.

Inactive ingredients

Titanium Dioxide, Water.

PRINCIPAL DISPLAY PANEL - 28 g Pencil Blister Pack

98472

HIS
A GENTLEMAN'S BRAND™

DURABLE
GROOMING
ESSENTIALS

STYPTIC PENCIL
ASTRINGENT

NET. WT. 28g (.9 oz.)

SATISFACTION GUARANTEED